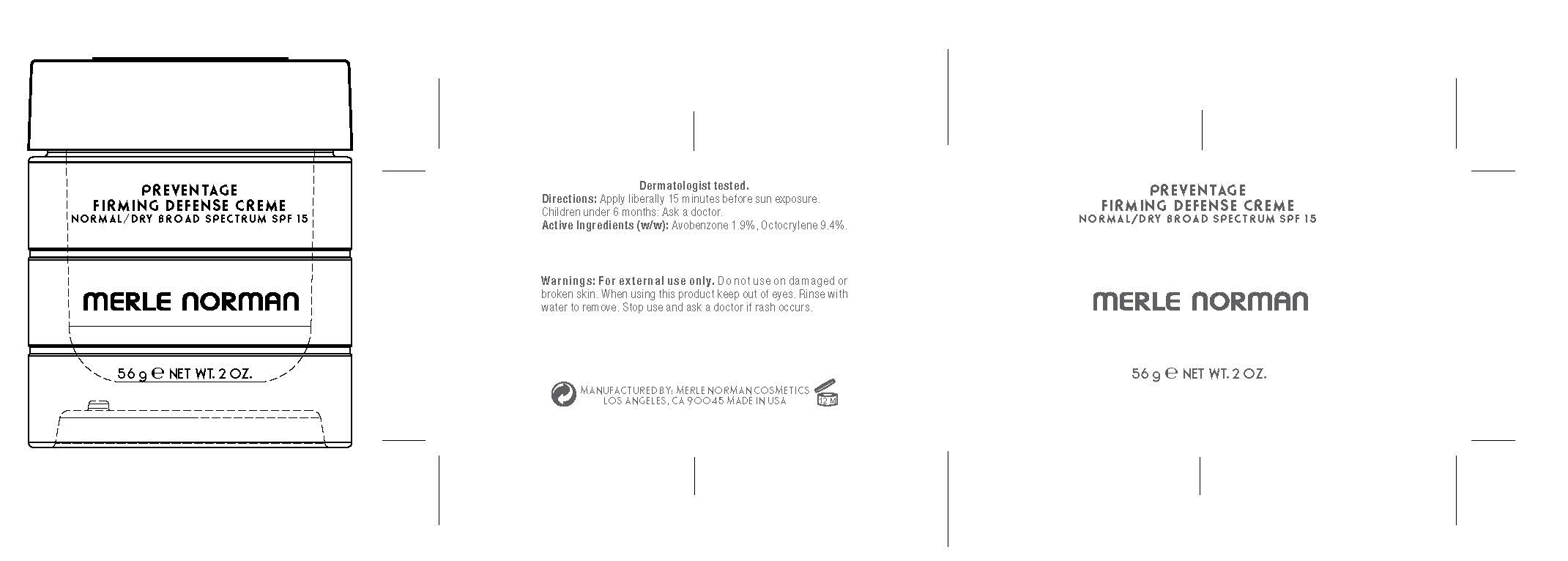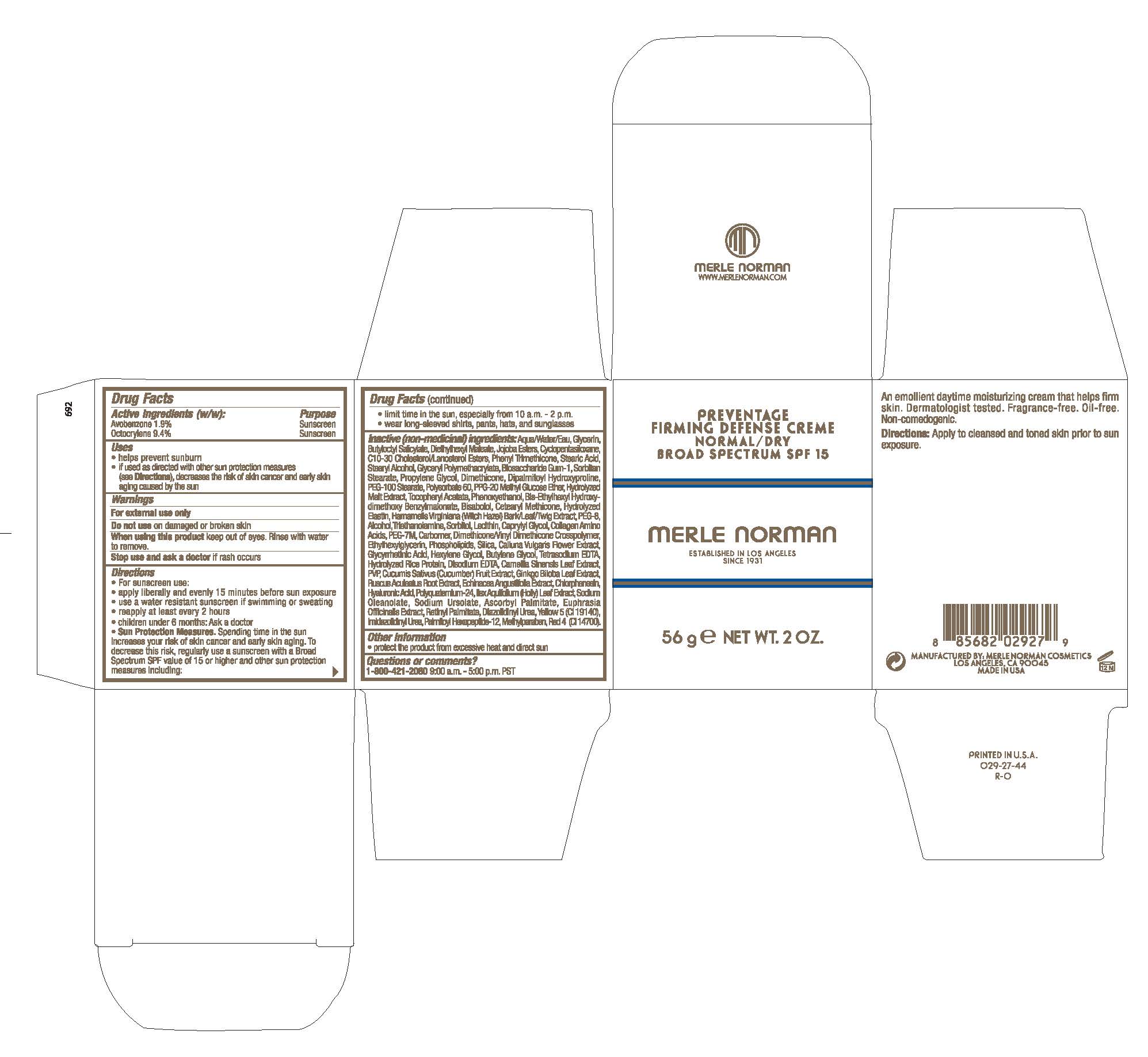 DRUG LABEL: Preventage Firming Defense Creme Normal/Dry Broad Spectrum SPF 15
NDC: 57627-203 | Form: CREAM
Manufacturer: Merle Norman Cosmetics, Inc.
Category: otc | Type: HUMAN OTC DRUG LABEL
Date: 20251119

ACTIVE INGREDIENTS: AVOBENZONE 1.9 g/100 g; OCTOCRYLENE 9.4 g/100 g
INACTIVE INGREDIENTS: SORBITOL; LECITHIN, SOYBEAN; CAPRYLYL GLYCOL; BUTYLOCTYL SALICYLATE; SORBITAN MONOSTEARATE; HEXYLENE GLYCOL; SILICON DIOXIDE; ETHYLHEXYLGLYCERIN; SODIUM URSOLATE; CHLORPHENESIN; DIMETHICONE/VINYL DIMETHICONE CROSSPOLYMER (HARD PARTICLE); CUCUMBER; TROLAMINE; GINKGO; ENOXOLONE; EDETATE DISODIUM ANHYDROUS; GREEN TEA LEAF; AMINO ACIDS; CARBOMER HOMOPOLYMER, UNSPECIFIED TYPE; DIETHYLHEXYL MALEATE; DIAZOLIDINYL UREA; FD&C RED NO. 4; WATER; PHENOXYETHANOL; POVIDONE; HYALURONIC ACID; SODIUM OLEANOLATE; C10-30 CHOLESTEROL/LANOSTEROL ESTERS; STEARYL ALCOHOL; BIOSACCHARIDE GUM-1; POLYSORBATE 60; HYDROLYZED BOVINE ELASTIN (BASE; 1000 MW); CYCLOMETHICONE 5; PHENYL TRIMETHICONE; STEARIC ACID; DIMETHICONE; PPG-20 METHYL GLUCOSE ETHER; ALPHA-TOCOPHEROL ACETATE; BUTYLENE GLYCOL; LEVOMENOL; CETEARYL METHICONE (15000 MW); DIPALMITOYL HYDROXYPROLINE; PEG-100 STEARATE; CALLUNA VULGARIS FLOWERING TOP; EDETATE SODIUM; METHYLPARABEN; GLYCERIN; BIS-ETHYLHEXYL HYDROXYDIMETHOXY BENZYLMALONATE; HAMAMELIS VIRGINIANA TOP; VITAMIN A PALMITATE; BASIC YELLOW 5; IMIDUREA; POLYETHYLENE OXIDE 300000; EUPHRASIA STRICTA; PALMITOYL HEXAPEPTIDE-12; PROPYLENE GLYCOL; ILEX AQUIFOLIUM LEAF; ASCORBYL PALMITATE; POLYETHYLENE GLYCOL 400; ALCOHOL; RUSCUS ACULEATUS ROOT; ECHINACEA ANGUSTIFOLIA

Preventage Firming Defense Creme Normal/Dry Broad Spectrum SPF 15

Active Ingredients (w/w): Purpose

Avobenzone 1.9% .........Sunscreen

Octocrylene 9.4% ......... Sunscreen

Uses

- helps prevent sunburn
- if used as directed with other sun protection measures (see DIrections), decreases the risk of skin cancer and early skin aging caused by the sun

Keep out of reach of children

Stop use and ask a doctor if rash occurs.

Directions

For sunscreen use:
apply liberally and evenly 15 minutes before sun exposure
use a water resistant sunscreen if swimming or sweating
reapply at least every 2 hours
children under 6 months: Ask a doctor
Sun Protection Measures. Spending time in the sun increases your risk of skin cancer and early skin aging. To decrease this risk, regularly use a sunscreen with a Broad Spectrum SPF value of 15 or higher and other sun protection measures including:
limit time in the sun, especially from 10 a.m. - 2 p.m.
wear long-sleeved shirts, pants, hats, and sunglasses
Apply to cleansed and toned skin prior to sun exposure

Warnings

For external use only

Do not use on damaged or broken skin

When using this product keep out of eyes. Rinse with water to remove.

INACTIVE INGREDIENT

Inactive (non-medicinal) ingredients: Aqua/Water/Eau, Glycerin, Butyloctyl Salicylate, Diethylhexyl Maleate, Jojoba Esters, Cyclopentasiloxane, C10-30 Cholesterol/Lanosterol Esters, Phenyl Trimethicone, Stearic Acid, Stearyl Alcohol, Glyceryl Polymethacrylate, Biosaccharide Gum-1, Sorbitan Stearate, Propylene Glycol, Dimethicone, Dipalmitoyl Hydroxyproline, PEG-100 Stearate, Polysorbate 60, PPG-20 Methyl Glucose Ether, Hydrolyzed Malt Extract, Tocopheryl Acetate, Phenoxyethanol, Bis-Ethylhexyl Hydroxydimethoxy Benzylmalonate, Bisabolol, Cetearyl Methicone, Hydrolyzed Elastin, Hamamelis Virginiana (Witch Hazel) Bark/Leaf/Twig Extract, PEG-8, Alcohol, Triethanolamine, Sorbital, Lecithin, Caprylyl Glycol, Collagen Amino Acids, PEG-7M, Carbomer, Dimethicone/Vinyl Dimethicone Crosspolymer, Ethylhexylglycerin, Phospholipids, Silica, Calluna Vulgaris Flower Extract, Glycyrrhethic Acid, Glycyrrhetinic Acid, Hexylene Glycol, Butylene Glycol, Tetrasodium EDTA, Hydrolyzed Rice Protein, Disodium EDTA, Camellia Sinensis Leaf Extract, PVP, Cucumis Sativus (Cucumber) Fruit Extract, Ginkgo Biloba Leaf Extract, Ruscus Aculeatus Root Extract, Echinacea angustifolia extract, Chlorphenesin, Hyaluronic Acid, Polyquaternium-24, Ilex Aquifolium (Holly) Leaf Extract, Sodium Oleanolate, Sodium Ursolate, Ascorbyl Palmitate, Euphrasia Officinalis Extract, Retinyl Palmitate, Diazolidinyl Urea, Yellow 5 (CI 19140), Imidazolidinyl Urea, Palmitoyl Hexapeptide-12, Methylparaben, Red 4 (CI 14700)

Other Information

- protect the product from excessive heat and direct sun